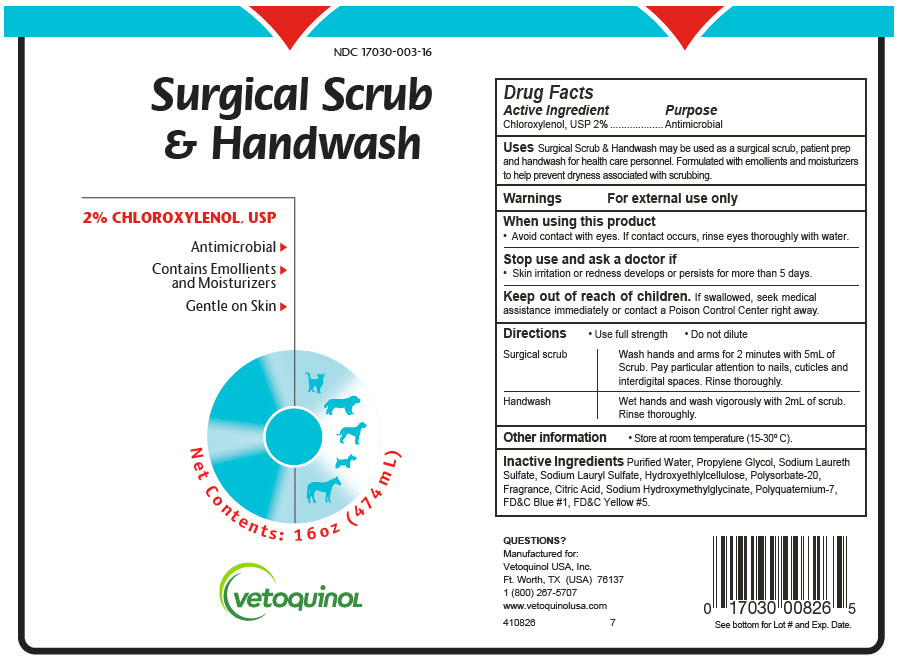 DRUG LABEL: SURGICAL SCRUB and HANDWASH
NDC: 17030-003 | Form: SOAP
Manufacturer: Vetoquinol USA, Inc.
Category: animal | Type: OTC ANIMAL DRUG LABEL
Date: 20221209

ACTIVE INGREDIENTS: Chloroxylenol 20 mg/1 mL
INACTIVE INGREDIENTS: WATER; PROPYLENE GLYCOL; SODIUM LAURETH-3 SULFATE; SODIUM LAURYL SULFATE; HYDROXYETHYL CELLULOSE, UNSPECIFIED; POLYSORBATE 20; CITRIC ACID MONOHYDRATE; SODIUM HYDROXYMETHYLGLYCINATE; POLYQUATERNIUM-7 (70/30 ACRYLAMIDE/DADMAC; 1600000 MW)

SURGICAL SCRUB & HANDWASH
2% CHLOROXYLENOL, USP

Drug Facts

Active Ingredient

Chloroxylenol, USP 2%

Purpose

Antimicrobial

INDICATIONS AND USAGE

Uses Surgical Scrub & Handwash may be used as a surgical scrub, patient prep and handwash for health care personnel. Formulated with emollients and moisturizers to help prevent dryness associated with scrubbing.

Warnings

For external use only

When using this product

- Avoid contact with eyes. If contact occurs, rinse eyes thoroughly with water.

Stop use and ask a doctor if

- Skin irritation or redness develops or persists for more than 5 days.

Keep out of reach of children. If swallowed, seek medical assistance immediately or contact a Poison Control Center right away.

Directions

- Use full strength
- Do not dilute

Surgical scrub | Wash hands and arms for 2 minutes with 5mL of Scrub. Pay particular attention to nails, cuticles and interdigital spaces. Rinse thoroughly.
Handwash | Wet hands and wash vigorously with 2mL of scrub. Rinse thoroughly.

Other information

- Store at room temperature (15-30° C).

Inactive Ingredients Purified Water, Propylene Glycol, Sodium Laureth Sulfate, Sodium Lauryl Sulfate, Hydroxyethlylcellulose, Polysorbate-20, Fragrance, Citric Acid, Sodium Hydroxymethylglycinate, Polyquaternium-7, FD&C Blue #1, FD&C Yellow #5.

QUESTIONS?

1 (800) 267-5707

PRINCIPAL DISPLAY PANEL - 474 mL Bottle Label

NDC 17030-003-16

Surgical Scrub
& Handwash

2% CHLOROXYLENOL, USP

Antimicrobial ▶

Contains Emollients ▶
and Moisturizers

Gentle on Skin ▶

Net Contents: 16oz (474 mL)

vetoquinoL